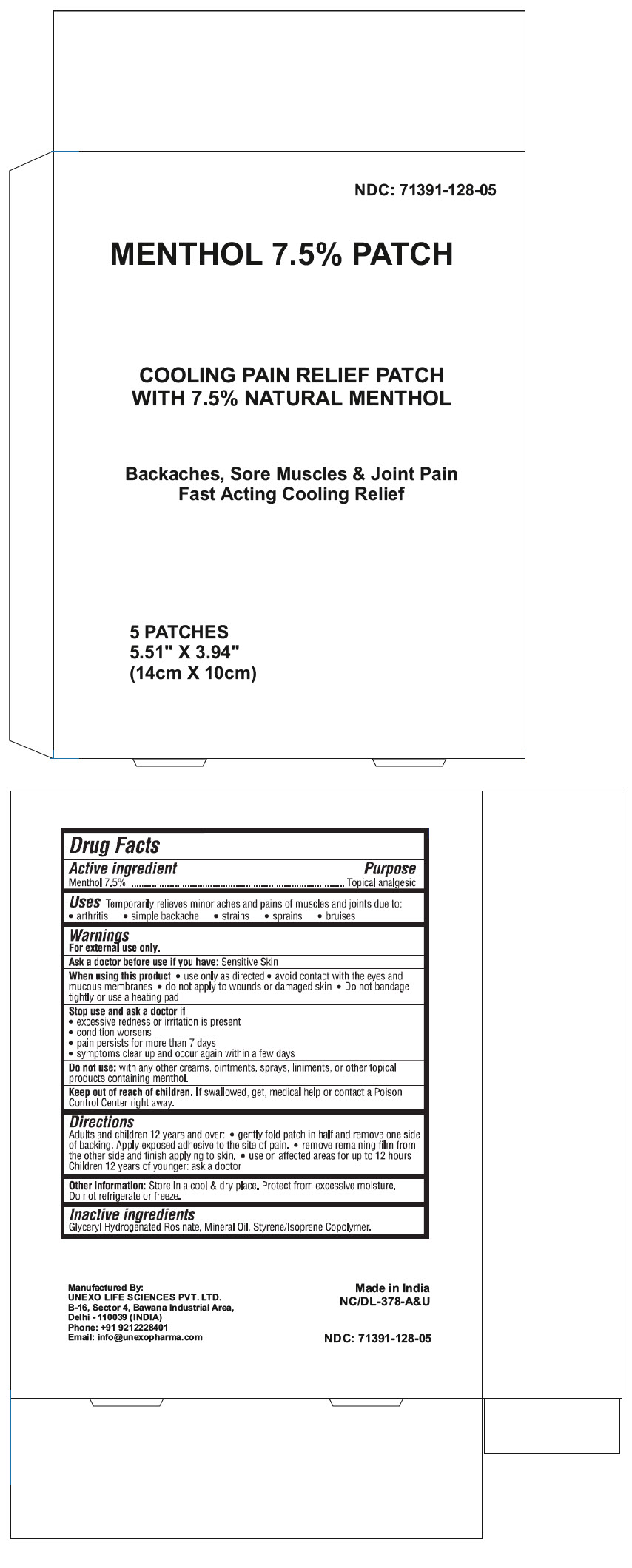 DRUG LABEL: Menthol
NDC: 71391-128 | Form: PATCH
Manufacturer: Unexo Life Sciences Private Limited
Category: otc | Type: HUMAN OTC DRUG LABEL
Date: 20250110

ACTIVE INGREDIENTS: MENTHOL, UNSPECIFIED FORM 105 mg/1 1
INACTIVE INGREDIENTS: GLYCEROL ESTER OF HYDROGENATED ROSIN; Mineral Oil; STYRENE/ISOPRENE/STYRENE BLOCK COPOLYMER

Menthol 7.5% Patch

Drug Facts

Active Ingredient

Menthol 7.5%

PURPOSE

Topical analgesic

Uses

Temporarily relieves minor aches and pains of muscles and joints due to:

- arthritis
- simple backache
- strains
- sprains
- bruises

Warnings

For external use only

Ask a doctor before use if you have

- Sensitive skin

When using this product

- Use only as directed
- Avoid contact with eyes and mucous membranes
- Do not apply to wounds or damaged skin
- Do not bandage tightly or use a heating pad

Stop use and ask a doctor if

- Excessive irritation or redness is present
- Condition worsens
- Pain persists for more than 7 days
- Symptom clear up and occur again within a few days

Do not use

- With other creams, ointments, sprays, liniments, or other topical products containing menthol.

Keep out of reach of children. If swallowed, get medical help or contact a Poison Control Center right away.

Directions

Adults and children over 12 years: Gently fold patch in half and remove one side of backing. Apply exposed adhesive to the site of pain. Remove remaining film from the other side and finish applying to skin. Use on affected areas for up to 12 hours. Children 12 years of age or younger: Consult a doctor

Other Information

Store in a cool & dry place. Protect from excessive moisture. Do not refrigerate or freeze.

Inactive Ingredients

Glyceryl Hydrogenated Rosinate, Mineral Oil, Styrene/Isoprene Copolymer

Questions or Comments

Call +91 9212228401

Manufactured By:

UNEXO LIFE SCIENCES PVT. LTD.
B-16. Sector 4, Bawana Industrial Area,
Delhi – 110039 (INDIA)

PRINCIPAL DISPLAY PANEL - 5 Patch Pouch Box

NDC: 71391-128-05

MENTHOL 7.5% PATCH

COOLING PAIN RELIEF PATCH
WITH 7.5% NATURAL MENTHOL

Backaches, Sore Muscles & Joint Pain
Fast Acting Cooling Relief

5 PATCHES
5.51" X 3.94"
(14cm X 10cm)